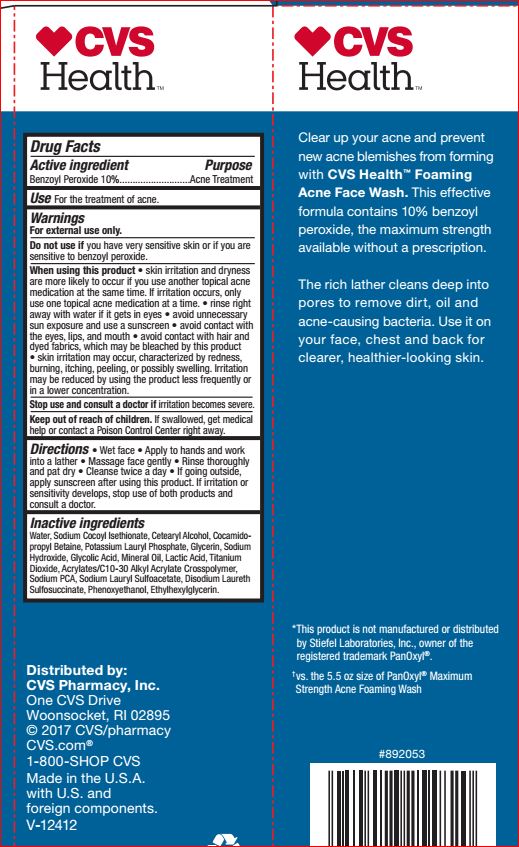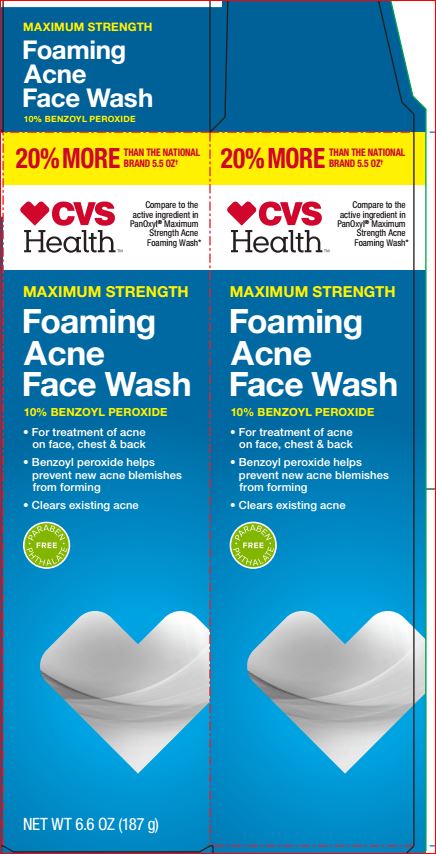 DRUG LABEL: Foamimg Acne Face Wash
NDC: 69842-666 | Form: CREAM
Manufacturer: CVS
Category: otc | Type: HUMAN OTC DRUG LABEL
Date: 20180424

ACTIVE INGREDIENTS: Benzoyl Peroxide 10 g/100 g
INACTIVE INGREDIENTS: CARBOMER INTERPOLYMER TYPE A (ALLYL SUCROSE CROSSLINKED); CETOSTEARYL ALCOHOL; Cocamidopropyl Betaine; Disodium Laureth Sulfosuccinate; Ethylhexylglycerin; Glycerin; Glycolic Acid; Lactic Acid; Mineral Oil; Phenoxyethanol; Potassium Lauryl Phosphate; Sodium Cocoyl Isethionate; Sodium Hydroxide; Sodium Lauryl Sulfoacetate; SODIUM PYRROLIDONE CARBOXYLATE; TITANIUM DIOXIDE; WATER

CVS Health
Drug Facts

Active ingredient Purpose
Benzoyl Peroxide 10%...........................Acne Treatment

INDICATIONS AND USAGE

Use For the treatment of acne

Warnings
For external use only.
Do not use if you have very sensitive skin or if you are
sensitive to benzoyl peroxide.
When using this product • skin irritation and dryness
are more likely to occur if you use another topical acne
medication at the same time. If irritation occurs, only
use one topical acne medication at a time. • rinse right
away with water if it gets in eyes • avoid unnecessary
sun exposure and use a sunscreen • avoid contact with
the eyes, lips, and mouth • avoid contact with hair and
dyed fabrics, which may be bleached by this product
• skin irritation may occur, characterized by redness,
burning, itching, peeling, or possibly swelling. Irritation
may be reduced by using the product less frequently or
in a lower concentration.
Stop use and consult a doctor if irritation becomes severe

DOSAGE AND ADMINISTRATION

Directions • Wet face • Apply to hands and work
into a lather • Massage face gently • Rinse thoroughly
and pat dry • Cleanse twice a day • If going outside,
apply sunscreen after using this product. If irritation or
sensitivity develops, stop use of both products and
consult a doctor.

Inactive ingredients
Water, Sodium Cocoyl Isethionate, Cetearyl Alcohol, Cocamidopropyl Betaine, Potassium Lauryl Phosphate, Glycerin, Sodium
Hydroxide, Glycolic Acid, Mineral Oil, Lactic Acid, Titanium
Dioxide, Acrylates/C10-30 Alkyl Acrylate Crosspolymer,
Sodium PCA, Sodium Lauryl Sulfoacetate, Disodium Laureth
Sulfosuccinate, Phenoxyethanol, Ethylhexylglycerin.